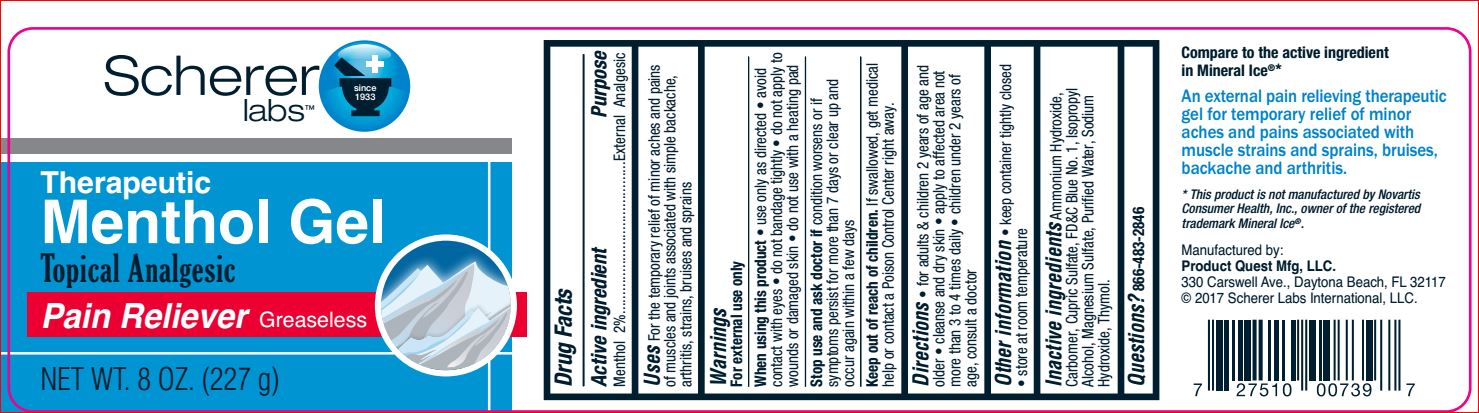 DRUG LABEL: Therapeutic Menthol
NDC: 64048-5117 | Form: GEL
Manufacturer: Product Quest Mfg
Category: otc | Type: HUMAN OTC DRUG LABEL
Date: 20180807

ACTIVE INGREDIENTS: Menthol 2 g/100 g
INACTIVE INGREDIENTS: AMMONIA; CARBOMER HOMOPOLYMER TYPE B (ALLYL SUCROSE CROSSLINKED); Cupric Sulfate; FD&C BLUE NO. 1; Isopropyl Alcohol; MAGNESIUM SULFATE, UNSPECIFIED FORM; WATER; Sodium Hydroxide; Thymol

Drug Facts

Active ingredient Purpose
Menthol 2%...........................................External Analgesic

Uses

For the temporary relief of minor aches and pains
of muscles and joints associated with simple backache,
arthritis, strains, bruises and sprains

Warnings
For external use only
When using this product • avoid
contact with eyes • do not bandage tightly • do not apply to
wounds or damaged skin • do not use with a heating pad
Stop use and ask doctor if condition worsens or if
symptoms persist for more than 7 days or clear up and
occur again within a few days
Keep out of reach of children. If swallowed, get medical
help or contact a Poison Control Center right away

Directions
• for adults & children 2 years of age and older
• cleanse and dry skin
• apply to affected area not more than 3 to 4 times daily
• children under 2 years of age, consult a doctor

Inactive ingredients

Ammonium Hydroxide,
Carbomer, Cupric Sulfate, FD&C Blue No. 1, Isopropyl
Alcohol, Magnesium Sulfate, Purified Water, Sodium
Hydroxide, Thymol.